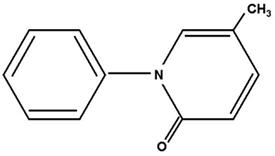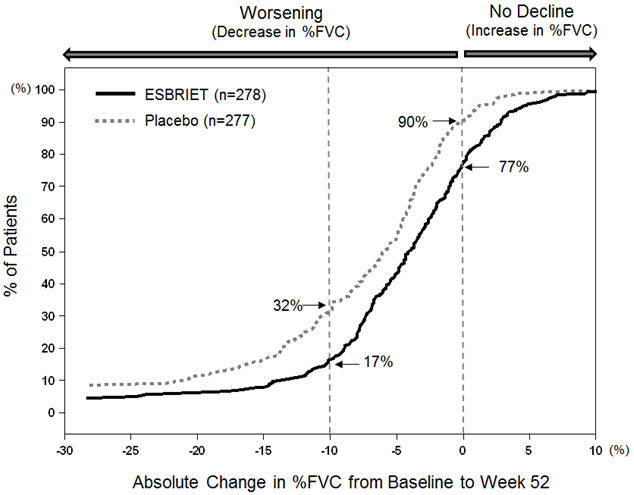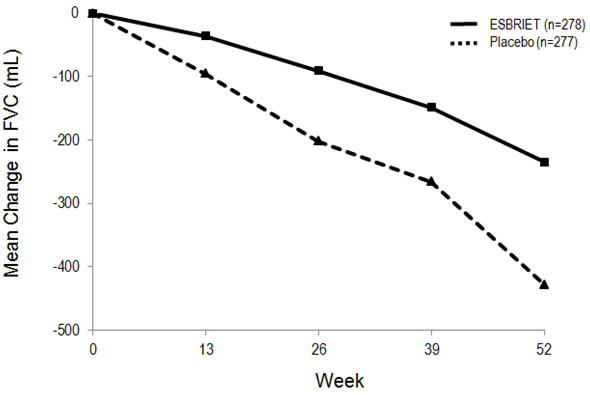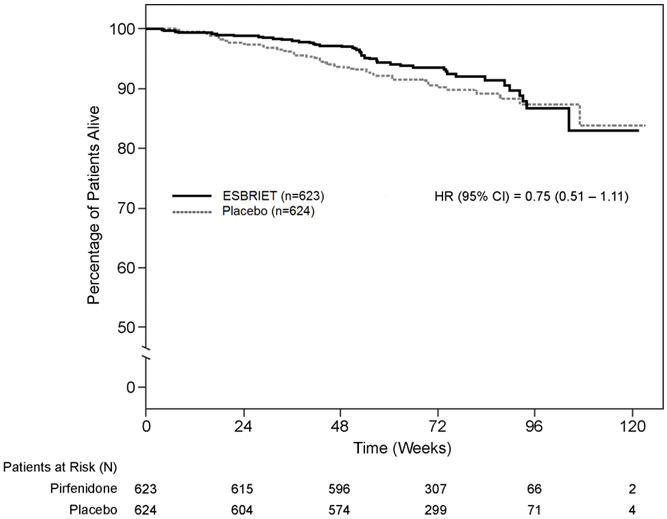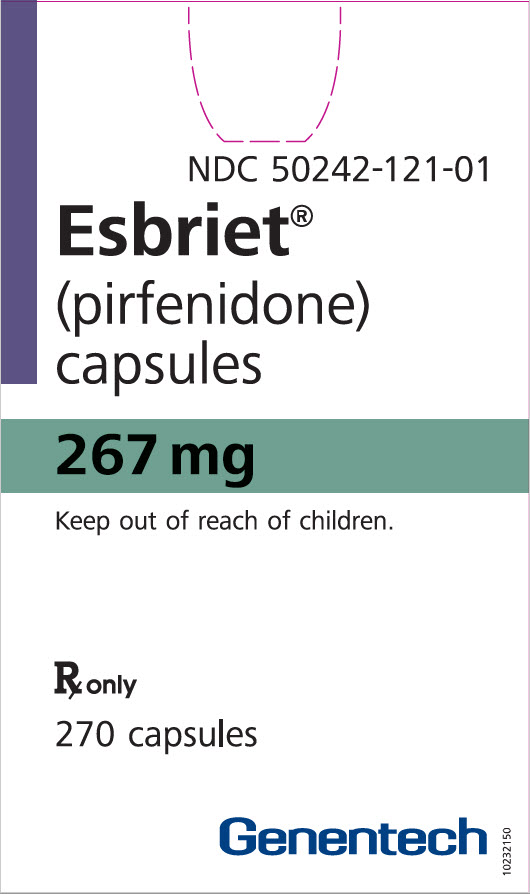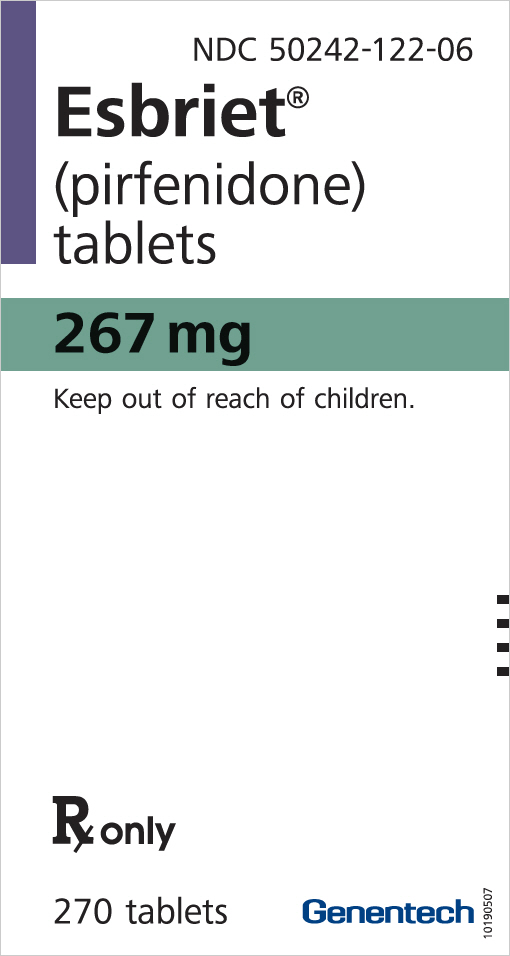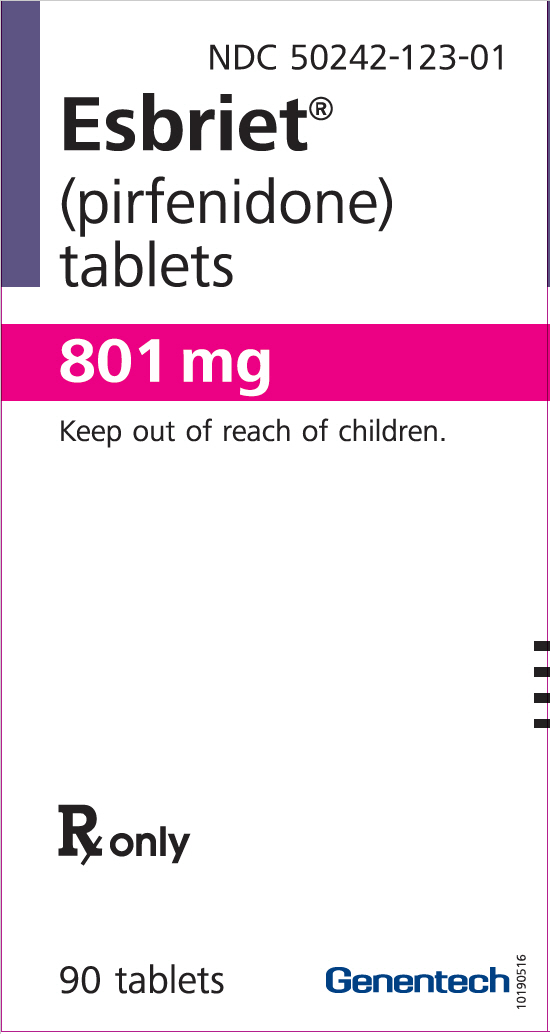 DRUG LABEL: ESBRIET
NDC: 50242-121 | Form: CAPSULE
Manufacturer: Genentech, Inc.
Category: prescription | Type: HUMAN PRESCRIPTION DRUG LABEL
Date: 20251205

ACTIVE INGREDIENTS: PIRFENIDONE 267 mg/1 1
INACTIVE INGREDIENTS: CROSCARMELLOSE SODIUM; MICROCRYSTALLINE CELLULOSE; POVIDONE, UNSPECIFIED; MAGNESIUM STEARATE; TITANIUM DIOXIDE; GELATIN, UNSPECIFIED; SHELLAC; FERROSOFERRIC OXIDE; FERRIC OXIDE RED; FERRIC OXIDE YELLOW; AMMONIA

HIGHLIGHTS OF PRESCRIBING INFORMATION

These highlights do not include all the information needed to use ESBRIET safely and effectively. See full prescribing information for ESBRIET.
ESBRIET® (pirfenidone) capsules and film-coated tablets, for oral use
Initial U.S. Approval: 2014

RECENT MAJOR CHANGES

Dosage and Administration (2.3) | 02/2023
Warnings and Precautions (5.3) | 02/2023

1 INDICATIONS AND USAGE

ESBRIET is a pyridone indicated for the treatment of idiopathic pulmonary fibrosis (IPF). (1)

2 DOSAGE AND ADMINISTRATION

- Take with food.
- Recommended dosage: 801 mg three times daily (2403 mg/day). (2)
- Upon initiation of treatment, titrate to the full dosage of 2403 mg/day over a 14-day period as follows:

Treatment days | Dosage
Days 1 through 7 | 267 mg three times daily (801 mg/day)
Days 8 through 14 | 534 mg three times daily (1602 mg/day)
Days 15 onward | 801 mg three times daily (2403 mg/day)

- Consider temporary dosage reduction, treatment interruption, or discontinuation for management of adverse reactions. (2.3, 5.1, 5.2, 5.3, 5.4)
- Prior to treatment, conduct liver function tests. (2.1)

3 DOSAGE FORMS AND STRENGTHS

- Capsules: 267 mg (3)
- Tablets: 267 mg, 801 mg (3)

4 CONTRAINDICATIONS

None

5 WARNINGS AND PRECAUTIONS

- Elevated liver enzymes and drug-induced liver injury: ALT, AST, and bilirubin elevations have occurred with ESBRIET including cases of drug-induced liver injury. In the postmarketing setting, non-serious and serious cases of drug-induced liver injury, including severe liver injury with fatal outcomes, have been reported. Monitor ALT, AST, and bilirubin before and during treatment. Temporary dosage reductions or discontinuations may be required. (2.1, 5.1)
- Photosensitivity and rash: Photosensitivity and rash have been noted with ESBRIET. Avoid exposure to sunlight and sunlamps. Wear sunscreen and protective clothing daily. Temporary dosage reductions or discontinuations may be required. (5.2)
- Severe Cutaneous Adverse Reactions (SCAR): Stevens-Johnson syndrome (SJS), toxic epidermal necrolysis (TEN), and drug reactions with eosinophilia and systemic symptoms (DRESS) have been reported in association with the use of ESBRIET in the postmarketing setting. Interrupt ESBRIET in case of signs or symptoms of SCAR. Permanently discontinue ESBRIET if a SCAR is confirmed. (5.3)
- Gastrointestinal disorders: Nausea, vomiting, diarrhea, dyspepsia, gastro-esophageal reflux disease, and abdominal pain have occurred with ESBRIET. Temporary dosage reductions or discontinuations may be required. (5.4)

6 ADVERSE REACTIONS

The most common adverse reactions (≥10%) are nausea, rash, abdominal pain, upper respiratory tract infection, diarrhea, fatigue, headache, decreased appetite, dyspepsia, dizziness, vomiting, gastro-esophageal reflux disease, sinusitis, insomnia, weight decreased, and arthralgia. (6.1)

To report SUSPECTED ADVERSE REACTIONS, contact Genentech at 1-888-835-2555 or FDA at 1-800-FDA-1088 or www.fda.gov/medwatch.

7 DRUG INTERACTIONS

Moderate (e.g., ciprofloxacin) and strong inhibitors of CYP1A2 (e.g., fluvoxamine) increase systemic exposure of ESBRIET and may alter the adverse reaction profile of ESBRIET. Discontinue fluvoxamine prior to administration of ESBRIET or reduce to 267 mg three times a day . Consider dosage reduction with use of ciprofloxacin. (7.1)

8 USE IN SPECIFIC POPULATIONS

- Hepatic Impairment: Monitor for adverse reactions and consider dosage modification or discontinuation of ESBRIET as needed. ESBRIET is not recommended for use in patients with severe hepatic impairment. (8.6, 12.3)
- Renal Impairment: Monitor for adverse reactions and consider dosage modification or discontinuation of ESBRIET as needed. ESBRIET is not recommended for use in patients with end stage renal disease on dialysis. (8.7, 12.3)
- Smokers: Decreased exposure has been noted in smokers which may alter the efficacy profile of ESBRIET. (8.8)

FULL PRESCRIBING INFORMATION

1 INDICATIONS AND USAGE

ESBRIET is indicated for the treatment of idiopathic pulmonary fibrosis (IPF).

2 DOSAGE AND ADMINISTRATION

2.1 Testing Prior to ESBRIET Administration

Conduct liver function tests prior to initiating treatment with ESBRIET [see Warnings and Precautions (5.1)].

2.2 Recommended Dosage

The recommended daily maintenance dosage of ESBRIET is 801 mg three times daily for a total of 2403 mg/day. Doses should be taken with food at the same time each day.

Upon initiation of treatment, titrate to the full dosage of 2403 mg/day over a 14-day period as follows:

Table 1. Dosage Titration for ESBRIET in Patients with IPF
Treatment days | Dosage
Days 1 through 7 | 267 mg three times daily (801 mg/day)
Days 8 through 14 | 534 mg three times daily (1602 mg/day)
Days 15 onward | 801 mg three times daily (2403 mg/day)

Dosages above 2403 mg/day are not recommended for any patient. Patients should not take 2 doses at the same time to make up for a missed dose. Patients should not take more than 3 doses per day.

2.3 Dosage Modifications due to Adverse Reactions

Patients who miss 14 or more days of ESBRIET should re-initiate treatment by undergoing the initial 2-week titration regimen up to the full maintenance dosage [see Dosage and Administration (2.2)]. For treatment interruption of less than 14 days, the dosage prior to the interruption can be resumed.

If patients experience significant adverse reactions (i.e., gastrointestinal, photosensitivity reaction or rash, severe cutaneous adverse reactions (SCAR)), consider temporary dosage reductions or interruptions of ESBRIET to allow for resolution of symptoms. If a SCAR is confirmed, permanently discontinue ESBRIET [see Warnings and Precautions (5.1, 5.2, 5.3, 5.4)].

Dosage Modification due to Elevated Liver Enzymes

Dosage modifications or interruptions may also be necessary when liver enzyme and bilirubin elevations are exhibited. For liver enzyme elevations, modify the dosage as follows:

If a patient exhibits >3 but ≤5 × the upper limit of normal (ULN) ALT and/or AST without symptoms or hyperbilirubinemia after starting ESBRIET therapy:

- Discontinue confounding medications, exclude other causes, and monitor the patient closely.
- Repeat liver chemistry tests as clinically indicated.
- The full daily dosage may be maintained, if clinically appropriate, or reduced or interrupted (e.g., until liver chemistry tests are within normal limits) with subsequent re-titration to the full dosage as tolerated.

If a patient exhibits >3 but ≤5 × ULN ALT and/or AST accompanied by symptoms or hyperbilirubinemia:

- Permanently discontinue ESBRIET.
- Do not rechallenge patient with ESBRIET.

If a patient exhibits >5 × ULN ALT and/or AST:

- Permanently discontinue ESBRIET.
- Do not rechallenge patient with ESBRIET.

2.4 Dosage Modification due to Drug Interactions

Strong CYP1A2 Inhibitors (e.g., fluvoxamine, enoxacin)

Reduce ESBRIET to 267 mg three times a day (801 mg/day).

Moderate CYP1A2 Inhibitors (e.g., ciprofloxacin)

With use of ciprofloxacin at a dosage of 750 mg twice daily, reduce ESBRIET to 534 mg three times a day (1602 mg/day).

3 DOSAGE FORMS AND STRENGTHS

Capsules: 267 mg, white to off-white, hard gelatin capsules printed with "PFD 267 mg" on the cap of the capsule in brown ink.

Film-coated tablets: oval, biconvex, debossed with "PFD", containing 267 mg (yellow) and 801 mg (brown) pirfenidone

4 CONTRAINDICATIONS

None.

5 WARNINGS AND PRECAUTIONS

5.1 Elevated Liver Enzymes and Drug-Induced Liver Injury

Cases of drug-induced liver injury (DILI) have been observed with ESBRIET. In the postmarketing period, non-serious and serious cases of DILI, including severe liver injury with fatal outcome, have been reported. Patients treated with Esbriet 2403 mg/day in three Phase 3 trials had a higher incidence of elevations in ALT or AST ≥3× ULN than placebo patients (3.7% vs 0.8%, respectively). Elevations ≥10×ULN in ALT or AST occurred in 0.3% of patients in the Esbriet 2403 mg/day group and in 0.2% of patients in the placebo group. Increases in ALT and AST ≥3× ULN were reversible with dose modification or treatment discontinuation.

Conduct liver function tests (ALT, AST, and bilirubin) prior to the initiation of therapy with ESBRIET, monthly for the first 6 months, every 3 months thereafter, and as clinically indicated. Measure liver function tests promptly in patients who report symptoms that may indicate liver injury, including fatigue, anorexia, right upper abdominal discomfort, dark urine, or jaundice. Dosage modification or interruption may be necessary for liver enzyme elevations [see Dosage and Administration (2.1, 2.3)].

5.2 Photosensitivity Reaction or Rash

Patients treated with ESBRIET 2403 mg/day in the three Phase 3 studies had a higher incidence of photosensitivity reactions (9%) compared with patients treated with placebo (1%). The majority of the photosensitivity reactions occurred during the initial 6 months. Instruct patients to avoid or minimize exposure to sunlight (including sunlamps), to use a sunblock (SPF 50 or higher), and to wear clothing that protects against sun exposure. Additionally, instruct patients to avoid concomitant medications known to cause photosensitivity. Dosage reduction or discontinuation may be necessary in some cases of photosensitivity reaction or rash [see Dosage and Administration (2.3)].

5.3 Severe Cutaneous Adverse Reactions

Severe cutaneous adverse reactions (SCAR), including Stevens-Johnson syndrome (SJS), toxic epidermal necrolysis (TEN), and drug reaction with eosinophilia and systemic symptoms (DRESS), have been reported in association with the use of ESBRIET in the postmarketing setting. If signs or symptoms of SCAR occur, interrupt ESBRIET treatment until the etiology of the reaction has been determined. Consultation with a dermatologist is recommended. If a SCAR is confirmed, permanently discontinue ESBRIET.

5.4 Gastrointestinal Disorders

In the clinical studies, gastrointestinal events of nausea, diarrhea, dyspepsia, vomiting, gastro-esophageal reflux disease, and abdominal pain were more frequently reported by patients in the ESBRIET treatment groups than in those taking placebo. Dosage reduction or interruption for gastrointestinal events was required in 18.5% of patients in the 2403 mg/day group, as compared to 5.8% of patients in the placebo group; 2.2% of patients in the ESBRIET 2403 mg/day group discontinued treatment due to a gastrointestinal event, as compared to 1.0% in the placebo group. The most common (>2%) gastrointestinal events that led to dosage reduction or interruption were nausea, diarrhea, vomiting, and dyspepsia. The incidence of gastrointestinal events was highest early in the course of treatment (with highest incidence occurring during the initial 3 months) and decreased over time. Dosage modifications may be necessary in some cases of gastrointestinal adverse reactions [see Dosage and Administration (2.3)].

6 ADVERSE REACTIONS

The following adverse reactions are discussed in greater detail in other sections of the labeling:

- Liver Enzyme Elevations and Drug-Induced Liver Injury [see Warnings and Precautions (5.1)]
- Photosensitivity Reaction or Rash [see Warnings and Precautions (5.2)]
- Severe Cutaneous Adverse Reactions [see Warnings and Precautions (5.3)]
- Gastrointestinal Disorders [see Warnings and Precautions (5.4)]

6.1 Clinical Trials Experience

Because clinical trials are conducted under widely varying conditions, adverse reaction rates observed in the clinical trials of a drug cannot be directly compared to rates in the clinical trials of another drug and may not reflect the rates observed in practice.

The safety of pirfenidone has been evaluated in more than 1400 subjects with over 170 subjects exposed to pirfenidone for more than 5 years in clinical trials.

ESBRIET was studied in 3 randomized, double-blind, placebo-controlled trials (Studies 1, 2, and 3) in which a total of 623 patients received 2403 mg/day of ESBRIET and 624 patients received placebo. Subjects ages ranged from 40 to 80 years (mean age of 67 years). Most patients were male (74%) and Caucasian (95%). The mean duration of exposure to ESBRIET was 62 weeks (range: 2 to 118 weeks) in these 3 trials.

At the recommended dosage of 2403 mg/day, 14.6% of patients on ESBRIET compared to 9.6% on placebo permanently discontinued treatment because of an adverse event. The most common (>1%) adverse reactions leading to discontinuation were rash and nausea. The most common (>3%) adverse reactions leading to dosage reduction or interruption were rash, nausea, diarrhea, and photosensitivity reaction.

The most common adverse reactions with an incidence of ≥10% and more frequent in the ESBRIET than placebo treatment group are listed in Table 2.

Table 2. Adverse Reactions Occurring in ≥10% of ESBRIET-Treated Patients and More Commonly Than Placebo in Studies 1, 2, and 3
Adverse Reaction | % of Patients (0 to 118 Weeks)
Adverse Reaction | ESBRIET 2403 mg/day (N = 623) | Placebo (N = 624)
Nausea | 36% | 16%
Rash | 30% | 10%
Abdominal Pain [Includes abdominal pain, upper abdominal pain, abdominal distension, and stomach discomfort.] | 24% | 15%
Upper Respiratory Tract Infection | 27% | 25%
Diarrhea | 26% | 20%
Fatigue | 26% | 19%
Headache | 22% | 19%
Decreased Appetite | 21% | 8%
Dyspepsia | 19% | 7%
Dizziness | 18% | 11%
Vomiting | 13% | 6%
Gastro-esophageal Reflux Disease | 11% | 7%
Sinusitis | 11% | 10%
Insomnia | 10% | 7%
Weight Decreased | 10% | 5%
Arthralgia | 10% | 7%

Adverse reactions occurring in ≥5 to <10% of ESBRIET-treated patients and more commonly than placebo are photosensitivity reaction (9% vs. 1%), pruritus (8% vs. 5%), asthenia (6% vs. 4%), dysgeusia (6% vs. 2%), and non-cardiac chest pain (5% vs. 4%).

6.2 Postmarketing Experience

In addition to adverse reactions identified from clinical trials the following adverse reactions have been identified during post-approval use of ESBRIET. Because these reactions are reported voluntarily from a population of uncertain size, it is not always possible to reliably estimate their frequency.

Blood and Lymphatic System Disorders: Agranulocytosis

Hepatobiliary Disorders: Drug-induced liver injury

Immune System Disorders: Angioedema

Skin and Subcutaneous Tissue Disorders: Severe Cutaneous Adverse Reactions (SCAR)

7 DRUG INTERACTIONS

7.1 CYP1A2 Inhibitors

Pirfenidone is metabolized primarily (70 to 80%) via CYP1A2 with minor contributions from other CYP isoenzymes including CYP2C9, 2C19, 2D6 and 2E1.

Strong CYP1A2 Inhibitors

The concomitant administration of ESBRIET and fluvoxamine or other strong CYP1A2 inhibitors (e.g., enoxacin) is not recommended because it significantly increases exposure to ESBRIET [see Clinical Pharmacology (12.3)]. Use of fluvoxamine or other strong CYP1A2 inhibitors should be discontinued prior to administration of ESBRIET and avoided during ESBRIET treatment. In the event that fluvoxamine or other strong CYP1A2 inhibitors are the only drug of choice, dosage reductions are recommended. Monitor for adverse reactions and consider discontinuation of ESBRIET as needed [see Dosage and Administration (2.4)].

Moderate CYP1A2 Inhibitors

Concomitant administration of ESBRIET and ciprofloxacin (a moderate inhibitor of CYP1A2) moderately increases exposure to ESBRIET [see Clinical Pharmacology (12.3)]. If ciprofloxacin at the dosage of 750 mg twice daily cannot be avoided, dosage reductions are recommended [see Dosage and Administration (2.4)]. Monitor patients closely when ciprofloxacin is used at a dosage of 250 mg or 500 mg once daily.

Concomitant CYP1A2 and other CYP Inhibitors

Agents or combinations of agents that are moderate or strong inhibitors of both CYP1A2 and one or more other CYP isoenzymes involved in the metabolism of ESBRIET (i.e., CYP2C9, 2C19, 2D6, and 2E1) should be discontinued prior to and avoided during ESBRIET treatment.

7.2 CYP1A2 Inducers

The concomitant use of ESBRIET and a CYP1A2 inducer may decrease the exposure of ESBRIET and this may lead to loss of efficacy. Therefore, discontinue use of strong CYP1A2 inducers prior to ESBRIET treatment and avoid the concomitant use of ESBRIET and a strong CYP1A2 inducer [see Clinical Pharmacology (12.3)].

8 USE IN SPECIFIC POPULATIONS

8.1 Pregnancy

Risk Summary

The data with ESBRIET use in pregnant women are insufficient to inform on drug associated risks for major birth defects and miscarriage. In animal reproduction studies, pirfenidone was not teratogenic in rats and rabbits at oral doses up to 3 and 2 times, respectively, the maximum recommended daily dose (MRDD) in adults [see Data].

In the U.S. general population, the estimated background risk of major birth defects and miscarriage in clinically recognized pregnancies is 2–4% and 15–20%, respectively.

Data

Animal Data

Animal reproductive studies were conducted in rats and rabbits. In a combined fertility and embryofetal development study, female rats received pirfenidone at oral doses of 0, 50, 150, 450, and 1000 mg/kg/day from 2 weeks prior to mating, during the mating phase, and throughout the periods of early embryonic development from gestation days (GD) 0 to 5 and organogenesis from GD 6 to 17. In an embryofetal development study, pregnant rabbits received pirfenidone at oral doses of 0, 30, 100, and 300 mg/kg/day throughout the period of organogenesis from GD 6 to 18. In these studies, pirfenidone at doses up to 3 and 2 times, respectively, the maximum recommended daily dose (MRDD) in adults (on mg/m^2 basis at maternal oral doses up to 1000 mg/kg/day in rats and 300 mg/kg/day in rabbits, respectively) revealed no evidence of impaired fertility or harm to the fetus due to pirfenidone. In the presence of maternal toxicity, acyclic/irregular cycles (e.g., prolonged estrous cycle) were seen in rats at doses approximately equal to and higher than the MRDD in adults (on a mg/m^2 basis at maternal doses of 450 mg/kg/day and higher). In a pre- and post-natal development study, female rats received pirfenidone at oral doses of 0, 100, 300, and 1000 mg/kg/day from GD 7 to lactation day 20. Prolongation of the gestation period, decreased numbers of live newborn, and reduced pup viability and body weights were seen in rats at an oral dosage approximately 3 times the MRDD in adults (on a mg/m^2 basis at a maternal oral dose of 1000 mg/kg/day).

8.2 Lactation

Risk Summary

No information is available on the presence of pirfenidone in human milk, the effects of the drug on the breastfed infant, or the effects of the drug on milk production. The lack of clinical data during lactation precludes clear determination of the risk of ESBRIET to an infant during lactation; therefore, the developmental and health benefits of breastfeeding should be considered along with the mother's clinical need for ESBRIET and the potential adverse effects on the breastfed child from ESBRIET or from the underlying maternal condition.

Data

Animal Data: A study with radio-labeled pirfenidone in rats has shown that pirfenidone or its metabolites are excreted in milk. There are no data on the presence of pirfenidone or its metabolites in human milk, the effects of pirfenidone on the breastfed child, or its effects on milk production.

8.4 Pediatric Use

Safety and effectiveness of ESBRIET in pediatric patients have not been established.

8.5 Geriatric Use

Of the total number of subjects in the clinical studies receiving ESBRIET, 714 (67%) were 65 years old and over, while 231 (22%) were 75 years old and over. No overall differences in safety or effectiveness were observed between older and younger patients. No dosage adjustment is required based upon age.

8.6 Hepatic Impairment

ESBRIET should be used with caution in patients with mild (Child Pugh Class A) to moderate (Child Pugh Class B) hepatic impairment. Monitor for adverse reactions and consider dosage modification or discontinuation of ESBRIET as needed [see Dosage and Administration (2.3)].

The safety, efficacy, and pharmacokinetics of ESBRIET have not been studied in patients with severe hepatic impairment. ESBRIET is not recommended for use in patients with severe (Child Pugh Class C) hepatic impairment [see Clinical Pharmacology (12.3)].

8.7 Renal Impairment

ESBRIET should be used with caution in patients with mild (CLcr 50–80 mL/min), moderate (CLcr 30–50 mL/min), or severe (CLcr less than 30 mL/min) renal impairment [see Clinical Pharmacology (12.3)]. Monitor for adverse reactions and consider dosage modification or discontinuation of ESBRIET as needed [see Dosage and Administration (2.3)]. The safety, efficacy, and pharmacokinetics of ESBRIET have not been studied in patients with end-stage renal disease requiring dialysis. Use of ESBRIET in patients with end-stage renal diseases requiring dialysis is not recommended.

8.8 Smokers

Smoking causes decreased exposure to ESBRIET [see Clinical Pharmacology (12.3)], which may alter the efficacy profile of ESBRIET. Instruct patients to stop smoking prior to treatment with ESBRIET and to avoid smoking when using ESBRIET.

10 OVERDOSAGE

There is limited clinical experience with overdosage. Multiple dosages of ESBRIET up to a maximum tolerated dose of 4005 mg per day were administered as five 267 mg capsules three times daily to healthy adult volunteers over a 12-day dose escalation.

In the event of a suspected overdosage, appropriate supportive medical care should be provided, including monitoring of vital signs and observation of the clinical status of the patient.

11 DESCRIPTION

ESBRIET belongs to the chemical class of pyridone. ESBRIET is available as a white to off-white hard gelatin capsule containing 267 mg of pirfenidone for oral administration, or, as film-coated tablets containing 267 mg (yellow) and 801 mg (brown) pirfenidone.

Pirfenidone has a molecular formula of C12H11NO and a molecular weight of 185.23. Pirfenidone has the following structural formula, which has been referred to as 5-methyl-1-phenyl-2-1(H)-pyridone or 5-methyl-1-phenyl-2-(1H)-pyridone.

Pirfenidone is a white to pale yellow, non-hygroscopic powder. It is more soluble in methanol, ethyl alcohol, acetone and chloroform than in water and 1.0 N HCl. The melting point is approximately 109°C.

ESBRIET capsule contains pirfenidone and the following inactive ingredients: microcrystalline cellulose, croscarmellose sodium, povidone, and magnesium stearate.

In addition, the capsule shell contains gelatin and titanium dioxide. The capsule brown printing ink includes shellac, iron oxide black, iron oxide red, iron oxide yellow, propylene glycol, ammonium hydroxide.

ESBRIET tablets contain pirfenidone and the following inactive ingredients: Microcrystalline cellulose, colloidal anhydrous silica, povidone, croscarmellose sodium, magnesium stearate, polyvinyl alcohol, titanium dioxide, macrogol (polyethylene glycol), talc, and iron oxide.

12 CLINICAL PHARMACOLOGY

12.1 Mechanism of Action

The mechanism of action of pirfenidone in the treatment of IPF has not been established.

12.2 Pharmacodynamics

Cardiac Electrophysiology:

The effect of ESBRIET on QT interval was evaluated in a randomized, placebo, and positive controlled parallel study in 160 healthy adult volunteers. Volunteers received ESBRIET 2403 mg/day (recommended dose) and 4005 mg/day (1.6 times recommended dose) or placebo for 10 days or a single dose of 400 mg moxifloxacin (active control).

Relative to placebo, the maximum mean change from baseline in study-specific QT interval was 3.2 milliseconds (ms) and 2.2 ms for ESBRIET 2403 mg/day and 4005 mg/day, respectively. No volunteer had a QTc interval greater than 480 ms or change from baseline greater than 60 ms. Although there was no evidence that ESBRIET prolonged the QTc interval in this study, a definitive conclusion may not be drawn as the positive control (moxifloxacin) did not perform as expected in this study, and ESBRIET at 4005 mg/day (1.7 times the maximum recommended dose) did not cover the maximum pirfenidone exposure increase with co-administration of fluvoxamine, a strong CYP1A2 inhibitor.

12.3 Pharmacokinetics

Absorption:

After single oral-dose administration of 801 mg ESBRIET (three 267 mg capsules), the maximum observed plasma concentration (Cmax) was achieved between 30 minutes and 4 hours (median time of 0.5 hours). Food decreased the rate and extent of absorption. Median Tmax increased from 0.5 hours to 3 hours with food. Maximum plasma concentrations (Cmax) and AUC0-inf decreased by approximately 49% and 16% with food, respectively.

Bioequivalence was demonstrated in the fasted state when comparing the 801 mg tablet to three 267 mg capsules. The effect of food on pirfenidone exposure was consistent between the tablet and capsule formulations.

A reduced incidence of adverse reactions was observed in the fed group when compared to the fasted group. In controlled studies with IPF patients, ESBRIET was taken with food [see Dosage and Administration (2) and Clinical Studies (14)].

The absolute bioavailability of pirfenidone has not been determined in humans.

Distribution:

ESBRIET binds to human plasma proteins, primarily to serum albumin, in a concentration-independent manner over the range of concentrations observed in clinical trials. The overall mean binding was 58% at concentrations observed in clinical studies (1 to 10 μg/mL). Mean apparent oral volume of distribution is approximately 59 to 71 liters.

Metabolism:

In vitro profiling studies in hepatocytes and liver microsomes have shown that ESBRIET is primarily metabolized in the liver by CYP1A2 and multiple other CYPs (CYP2C9, 2C19, 2D6, and 2E1). Oral administration of ESBRIET results in the formation of four metabolites. In humans, only pirfenidone and 5-carboxy-pirfenidone are present in plasma in significant quantities. The mean metabolite-to-parent ratio ranged from approximately 0.6 to 0.7.

No formal radiolabeled studies have assessed the metabolism of pirfenidone in humans. In vitro data suggests that metabolites are not expected to be pharmacologically active at observed metabolite concentrations.

Elimination:

The mean terminal half-life is approximately 3 hours in healthy subjects. Pirfenidone is excreted predominantly as metabolite 5-carboxy-pirfenidone, mainly in the urine (approximately 80% of the dose). The majority of ESBRIET was excreted as the 5-carboxy metabolite (approximately 99.6% of that recovered).

Specific Populations:

Hepatic Impairment

The pharmacokinetics of ESBRIET and the 5-carboxy-pirfenidone metabolite were studied in 12 subjects with moderate hepatic impairment (Child Pugh Class B) and in 12 subjects with normal hepatic function. Results showed that the mean exposure, AUC0-inf and Cmax of pirfenidone increased approximately 1.6- and approximately 1.4-fold in subjects with moderate hepatic impairment, respectively. The exposure of 5-carboxy-pirfenidone did not change significantly in subjects with moderate hepatic impairment.

Renal Impairment

The pharmacokinetics of pirfenidone and the 5-carboxy-pirfenidone metabolite were studied in 18 subjects with mild (CLcr 50 to 80 mL/min), moderate (CLcr 30 to 50 mL/min), and severe (CLcr less than 30 mL/min) renal impairment (n=6/group) and in 6 subjects with normal CLcr (greater than or equal to 80 mL/min) renal function. Results showed that systemic exposure (AUC0-inf) to pirfenidone increased approximately 1.4, 1.5, and 1.2-fold in subjects with mild, moderate and severe renal impairment, respectively. The corresponding AUC0-inf of 5-carboxy-pirfenidone increased 1.7, 3.4, and 5.6-fold, although the change in the patients with mild renal impairment was not statistically significant. The renal clearance of 5-carboxy-pirfenidone decreased significantly in patients with moderate to severe renal impairment.

The pharmacokinetics and safety of ESBRIET has not been studied in subjects with end-stage renal disease requiring dialysis.

Geriatric

Results of population pharmacokinetic analysis suggest that no dosage adjustment is needed in geriatric patients.

Gender

Results of population pharmacokinetic analysis of ESBRIET showed no significant differences in pharmacokinetics between males and females.

Obesity

Results of population pharmacokinetic analysis showed that obesity (Body Mass Index [BMI] greater than or equal to 30 kg/m^2) has no significant effect on the pharmacokinetics of ESBRIET.

Race

Population pharmacokinetic analysis showed that race has no significant effect on the pharmacokinetics of pirfenidone.

Drug Interaction Studies:

Cytochrome P450 1A2 Inhibitors

Pirfenidone is a substrate of cytochrome P450 1A2. In a single-dose drug interaction study in 25 healthy nonsmokers and 25 smokers, ESBRIET was coadministered with fluvoxamine (50 mg at bedtime for 3 days; 50 mg twice a day for 3 days, and 50 mg in the morning and 100 mg at bedtime for 4 days). An approximately 4-fold increase in exposure to pirfenidone in nonsmokers and approximately 7-fold increase in exposure in smokers was observed.

In a single-dose drug interaction study in 27 healthy subjects, coadministration of 801 mg of ESBRIET and 750 mg of ciprofloxacin (a moderate inhibitor of CYP1A2) on Day 6 (ciprofloxacin was dosed at 750 mg twice daily from Day 2 to Day 7) increased the exposure to pirfenidone by 81%.

Cytochrome P450 1A2 Inducers

Following a single oral dose of 801 mg ESBRIET in 25 smokers and 25 healthy nonsmokers, the systemic exposure in smokers was significantly lower compared to nonsmokers. AUC0-inf and Cmax of pirfenidone in smokers were 46% and 68% of those in nonsmokers, respectively.

Inhibitory Effect of Pirfenidone on P-glycoprotein (Pgp)

The potential for pirfenidone to inhibit Pgp mediated transport of digoxin (5.0 µM) was evaluated in the absence and presence of pirfenidone at concentrations ranging from 1 to 1000 µM in in vitro system. Pirfenidone showed weak inhibition (10 to 30%) of Pgp facilitated digoxin B-A efflux at concentrations of 100 µM and above. Effect of pirfenidone upon Pgp substrate pharmacokinetics and safety has not been evaluated in humans.

Inhibitory Effect of Pirfenidone on CYP2C9, 2C19 or 1A2, 2D6, 3A4

The potential for pirfenidone to inhibit CYP2C9, 2C19 or 1A2 was evaluated in vitro at concentrations up to 1000 µM (approximately 10-fold the mean human Cmax). Pirfenidone showed a concentration-dependent inhibition on CYP2C9, 2C19 or 1A2, 2D6, and 3A4. At 1000 µM, pirfenidone inhibits the activity of these enzymes by 30.4%, 27.5%, 34.1%, 21%, and 9.6%, respectively. Effect of pirfenidone upon pharmacokinetics and safety of CYP2C9, 2C19, 1A2, 2D6, and 3A4 substrates has not been evaluated in humans.

13 NONCLINICAL TOXICOLOGY

13.1 Carcinogenesis, Mutagenesis, Impairment of Fertility

Carcinogenesis

Long-term studies were conducted in mice and rats with admixture of pirfenidone to the diet to evaluate its carcinogenic potential.

In a 24-month carcinogenicity study in B6C3F1 mice, pirfenidone caused statistically significant dose-related increases of the combination of hepatocellular adenoma and carcinoma and hepatoblastoma in male mice at doses of 800 mg/kg and above (AUC exposure approximately 0.4 times adult exposure at the MRDD). There were statistically significant dose-related increases of the combination of hepatocellular adenoma and carcinoma in female mice at doses of 2000 mg/kg and above (AUC exposure approximately 0.7 times adult exposure at the MRDD).

In a 24-month carcinogenicity study in Fischer rats, pirfenidone caused statistically significant dose-related increases of the combination of hepatocellular adenoma and carcinoma in male rats at doses of 750 mg/kg and above (AUC exposure approximately 1.9 times adult exposure at the MRDD). There were statistically significant increases of the combination of hepatocellular adenoma and carcinoma and the combination of uterine adenocarcinoma and adenoma at a dose of 1500 mg/kg/day (AUC exposure approximately 3.0 times adult exposure at the MRDD).

The relevance of these tumor findings in rodents to humans is unknown.

Mutagenesis

Pirfenidone was not mutagenic or clastogenic in the following tests: mutagenicity tests in bacteria, a chromosomal aberration test in Chinese hamster lung cells, and a micronucleus test in mice.

Impairment of Fertility

Pirfenidone had no effects on fertility and reproductive performance in rats at dosages up to 1000 mg/kg/day (approximately 3 times the MRDD in adults on a mg/m^2 basis).

14 CLINICAL STUDIES

The efficacy of ESBRIET was evaluated in patients with IPF in three phase 3, randomized, double-blind, placebo-controlled, multicenter trials (Studies 1, 2, and 3).

Study 1 was a 52-week trial comparing ESBRIET 2403 mg/day (n=278) versus placebo (n=277) in patients with IPF. Study 2 and Study 3 were nearly identical to each other in design, with few exceptions, including an intermediate dose treatment arm in Study 2. Study 2 compared treatment with either ESBRIET 2403 mg/day (n=174) or ESBRIET 1197 mg/day (n=87) to placebo (n=174), while Study 3 compared ESBRIET 2403 mg/day (n=171) to placebo (n=173). Study drug was administered three times daily with food for a minimum of 72 weeks. Patients continued on treatment until the last patient completed 72 weeks of treatment, which included observations to approximately 120 weeks of study treatment. The primary endpoint was the change in percent predicted forced vital capacity (%FVC) from baseline to study end, measured at 52 weeks in Study 1, and at 72 weeks in Studies 2 and 3.

Studies 1, 2 and 3 enrolled adult patients who had a clinical and radiographic diagnosis of IPF (with or without accompanying surgical lung biopsy), without evidence or suspicion of an alternative diagnosis for interstitial lung disease. Eligible patients were to have %FVC greater than or equal to 50% at baseline and a percent predicted diffusing capacity of the lungs for carbon monoxide (%DLCO) greater than or equal to 30% (Study 1) or 35% (Studies 2 and 3) at baseline. In all three trials, over 80% of patients completed study treatment.

A total of 1247 patients with IPF were randomized to receive ESBRIET 2403 mg/day (n=623) or placebo (n=624) in these three trials. Baseline characteristics were generally balanced across treatment groups. The study population ranged from 40 to 80 years of age (mean age 67 years). Most patients were male (74%), white (95%), and current or former smokers (65%). Approximately 93% of patients met criteria for definite IPF on high resolution computed tomography (HRCT). Baseline mean %FVC and %DLCO were 72% and 46%, respectively. Approximately 15% subjects discontinued from each treatment group.

Change from Baseline in Percent Predicted Forced Vital Capacity

In Study 1, the primary efficacy analysis for the change in %FVC from baseline to Week 52 demonstrated a statistically significant treatment effect of ESBRIET 2403 mg/day (n=278) compared with placebo (n=277) using a rank ANCOVA with the lowest rank imputation for missing data due to death. In Study 2, there was a statistically significant difference at Week 72 for the change in %FVC from baseline. In Study 3, there was no statistically significant difference at Week 72 for the change in %FVC from baseline.

Figure 1 presents the cumulative distribution for all cut-offs for the change from baseline in %FVC at Week 52 for Study 1. For all categorical declines in lung function, the proportion of patients declining was lower on ESBRIET than on placebo. Study 2 showed similar results.

Figure 1. Cumulative Distribution of Patients by Change in Percent Predicted FVC from Baseline to Week 52 (Study 1). The Dashed Lines Indicate ≥10% Decline or ≥0% Decline.

Mean Change from Baseline in FVC (mL)

In Study 1, a reduction in the mean decline in FVC (in mL) was observed in patients receiving ESBRIET 2403 mg/day (-235 mL) compared to placebo (-428 mL) (mean treatment difference 193 mL) at Week 52 (see Figure 2). In Study 2, a reduction in the decline in FVC volume was also observed in patients receiving ESBRIET 2403 mg/day compared with placebo (mean treatment difference 157 mL) at Week 72. There was no statistically significant difference in decline in FVC volume seen in Study 3.

Figure 2. Mean Change from Baseline in Forced Vital Capacity (Study 1)

Survival

Survival was evaluated for ESBRIET compared to placebo in Studies 1, 2, and 3 as an exploratory analysis to support the primary endpoint (FVC). All-cause mortality was assessed over the study duration and available follow-up period, irrespective of cause of death and whether patients continued treatment. All-cause mortality did not show a statistically significant difference (see Figure 3).

Figure 3. Kaplan-Meier Estimates of All-Cause Mortality at Vital Status – End of Study: Studies 1, 2, and 3

16 HOW SUPPLIED/STORAGE AND HANDLING

ESBRIET white to off-white hard gelatin capsules contain 267 mg of pirfenidone. The cap of the capsule is printed with "PFD 267 mg" in brown ink. The capsule is supplied either in a bottle, a 14-day titration blister pack or a 4-week maintenance blister pack.

ESBRIET film-coated tablets are oval, biconvex, debossed with "PFD", containing 267 mg (yellow) and 801 mg (brown) pirfenidone. The film-coated tablets are supplied in bottles.

ESBRIET capsules:

- NDC 50242-121-01, bottle for a 30-day supply containing 270 capsules and closed with a child-resistant closure
- NDC 50242-121-02, 14-day titration blister pack, carton containing a total of 63 capsules in two blister cards – a Week 1 blister card containing 21 capsules (1 capsule per blister well) and a Week 2 blister card containing 42 capsules (2 capsules per blister well)
- NDC 50242-121-03, 4-week maintenance blister pack, carton containing a total of 252 capsules in four blister cards each with 63 capsules (3 capsules per blister well)

ESBRIET film-coated tablets:

- NDC 50242-122-05, carton containing 3 bottles, each containing ninety 267 mg tablets (270 tablets total) with a child-resistant closure
- NDC 50242-122-06, carton containing 1 bottle containing 270 tablets, 267 mg each, with a child-resistant closure
- NDC 50242-123-01, carton containing 1 bottle containing ninety 801 mg tablets, with a child-resistant closure

STORAGE AND HANDLING

Store at 25°C (77°F); excursions permitted to 15–30°C (59–86°F) (see USP Controlled Room Temperature).

Keep the bottle tightly closed. Do not use if the seal over the bottle opening is broken or missing. Safely throw away any ESBRIET that is out of date or no longer needed.

17 PATIENT COUNSELING INFORMATION

Advise the patient to read the FDA-approved patient labeling (Patient Information).

Liver Enzyme Elevations

Advise patients that they may be required to undergo liver function testing periodically. Instruct patients to immediately report any symptoms of a liver problem (e.g., skin or the white of eyes turn yellow, urine turns dark or brown [tea colored], pain on the right side of stomach, bleed or bruise more easily than normal, lethargy) [see Warnings and Precautions (5.1)].

Photosensitivity Reaction or Rash

Advise patients to avoid or minimize exposure to sunlight (including sunlamps) during use of ESBRIET because of concern for photosensitivity reactions or rash. Instruct patients to use a sunblock and to wear clothing that protects against sun exposure. Instruct patients to report symptoms of photosensitivity reaction or rash to their physician. Temporary dosage reductions or discontinuations may be required [see Warnings and Precautions (5.2)].

Severe Cutaneous Adverse Reactions

Advise patients about signs and symptoms of severe cutaneous adverse reactions (SCAR). Advise patients to contact their healthcare provider immediately if they experience signs and symptoms of SCAR [see Warnings and Precautions (5.3)].

Gastrointestinal Events

Instruct patients to report symptoms of persistent gastrointestinal effects including nausea, diarrhea, dyspepsia, vomiting, gastro-esophageal reflux disease, and abdominal pain. Temporary dosage reductions or discontinuations may be required [see Warnings and Precautions (5.4)].

Smokers

Encourage patients to stop smoking prior to treatment with ESBRIET and to avoid smoking when using ESBRIET [see Clinical Pharmacology (12.3)].

Take with Food

Instruct patients to take ESBRIET with food to help decrease nausea and dizziness.

Distributed by:
Genentech USA, Inc.
A Member of the Roche Group
1 DNA Way
South San Francisco, CA 94080-4990

ESBRIET® is a registered U.S. trademark of Genentech, Inc.
© 2023 Genentech USA, Inc.

Patient Information
ESBRIET (es-BREE-et)
(pirfenidone)
capsules and film-coated tablets
What is ESBRIET?
- ESBRIET is a prescription medicine used to treat people with a lung disease called idiopathic pulmonary fibrosis (IPF).
- It is not known if ESBRIET is safe and effective in children.
Before you take ESBRIET, tell your doctor about all of your medical conditions, including if you:
- have liver problems
- have kidney problems
- are a smoker
- are pregnant or plan to become pregnant. It is not known if ESBRIET will harm your unborn baby.
- are breastfeeding or plan to breastfeed. It is not known if ESBRIET passes into your breast milk. You and your doctor should decide if you will take ESBRIET.
Tell your doctor about all the medicines you take, including prescription and over-the-counter medicines, vitamins, and herbal supplements.
How should I take ESBRIET?
- Take ESBRIET exactly as your doctor tells you to take it.
- Your doctor may change your dose of ESBRIET as needed.
- Take ESBRIET with food at the same time each day. This may help to decrease your nausea and dizziness.
  - ESBRIET 267 mg is supplied as either a white to off-white capsule or a yellow tablet. If you have been prescribed ESBRIET 267 mg, take it as follows:
    - Take 1 ESBRIET 267 mg capsule or tablet 3 times each day for days 1 through 7.
    - Take 2 ESBRIET 267 mg capsule or tablet 3 times each day for days 8 through 14.
    - Take 3 ESBRIET 267 mg capsule or tablet 3 times each day on day 15 and each day after.
 | Esbriet 267 mg Dosing Schedule
 | Week | Morning (Breakfast) | Afternoon (Lunch) | Evening (Dinner) | Total Pills Each Day
 | Days 1-7 | 1 | 1 | 1 | 3
 | Days 8-14 | 2 | 2 | 2 | 6
 | Days 15 onward | 3 | 3 | 3 | 9
 | - If you have been prescribed the brown 801 mg ESBRIET film-coated tablets, take it as follows: - Take 1 brown 801 mg ESBRIET tablet 3 times each day.
 | Esbriet 801 mg Dosing Schedule
 | Week | Morning (Breakfast) | Afternoon (Lunch) | Evening (Dinner) | Total Pills Each Day
 | Days 15 onward | 1 | 1 | 1 | 3
- If you miss 14 days or more of ESBRIET call your doctor right away for further instructions about how to take your medicine.
- Do not take 2 doses at the same time to make up for your missed dose.
- Do not take more than 3 doses each day.
- If you take too much ESBRIET, call your doctor or go to the nearest hospital emergency room right away.
- Your doctor should do certain blood tests before you start taking ESBRIET.
What should I avoid while taking ESBRIET?
- Avoid sunlight. ESBRIET can make your skin sensitive to the sun and the light from sunlamps and tanning beds. You could get a severe sunburn. Use sunscreen (SPF 50) and wear a hat and clothes that cover your skin if you have to be in sunlight. Talk to your doctor if you get sunburn or a rash.
- Avoid taking ESBRIET with other medicines that can make your skin sensitive to the sun, the light from sunlamps and tanning beds.
- Avoid smoking. Smoking may affect how well ESBRIET works.
What are the possible side effects of ESBRIET?
ESBRIET may cause serious side effects, including:
- liver problems. Call your doctor right away if you have unexplained symptoms such as yellowing of your skin or the white part of your eyes (jaundice), dark or brown (tea colored) urine, pain on the upper right side of your stomach area (abdomen), bleeding or bruising more easily than normal, feeling tired.
  Your doctor will do blood tests to check how your liver is working during your treatment with ESBRIET.
- sensitivity to sunlight (photosensitivity) and rash. See "What should I avoid while taking ESBRIET?"
- severe skin reactions. Call your doctor right away if you have a severe skin reaction such as skin blisters, rash, sores in the mouth, hives or any other severe skin symptoms. Your doctor may stop your treatment with ESBRIET.
- stomach problems. ESBRIET may cause stomach problems such as nausea, vomiting, diarrhea, indigestion, heartburn, and stomach pain. Tell your doctor right away if your stomach problems get worse or do not go away. Your doctor may need to change your dose of ESBRIET.
The most common side effects of ESBRIET include feeling tired, insomnia, upper respiratory tract infections, sinusitis, headache, dizziness, decreased weight and decreased or loss of appetite.
These are not all the possible side effects of ESBRIET. Call your doctor for medical advice about side effects. You may report side effects to FDA at 1-800-FDA-1088.
How should I store ESBRIET?
- Store ESBRIET capsules and tablets at room temperature, 77°F (25°C).
- Keep in a tightly closed container.
Safely throw away any ESBRIET that is out of date or no longer needed. Keep ESBRIET and all medicines out of reach of children.
General information about the safe and effective use of ESBRIET.
Medicines are sometimes prescribed for purposes other than those listed in a Patient Information leaflet. Do not use ESBRIET for a condition for which it was not prescribed. Do not give ESBRIET to other people, even if they have the same symptoms that you have. It may harm them. You can ask your pharmacist or doctor for information about ESBRIET that is written for health professionals.
What are the ingredients in ESBRIET capsules?
Active ingredient: pirfenidone
Inactive ingredients: microcrystalline cellulose, croscarmellose sodium, povidone, and magnesium stearate
Capsule Shell: gelatin and titanium dioxide
Capsule Brown Printing Ink: shellac, iron oxide black, iron oxide red, iron oxide yellow, propylene glycol, ammonium hydroxide
What are the ingredients in ESBRIET film-coated tablets?
Active ingredient: pirfenidone
Inactive ingredients: microcrystalline cellulose, colloidal anhydrous silica, povidone, croscarmellose sodium, magnesium stearate, polyvinyl alcohol, titanium dioxide, macrogol (polyethylene glycol), talc, and iron oxide
For more information, go to www.ESBRIET.com or call 1-888-835-2555.
© 2023 Genentech USA, Inc.
This Patient Information has been approved by the U.S. Food and Drug Administration |  |  |  |  |  | Revised: February 2023

Representative sample of labeling (see the HOW SUPPLIED section for complete listing):

PRINCIPAL DISPLAY PANEL - 267 mg Capsule Bottle Carton

NDC 50242-121-01

Esbriet®
(pirfenidone)
capsules

267 mg

Keep out of reach of children.

Rx only
270 capsules

Genentech

10232150

PRINCIPAL DISPLAY PANEL - 267 mg Tablet Bottle Carton

NDC 50242-122-06

Esbriet®
(pirfenidone)
tablets

267 mg

Keep out of reach of children.

Rx only

270 tablets
Genentech

10190507

PRINCIPAL DISPLAY PANEL - 801 mg Tablet Bottle Carton

NDC 50242-123-01

Esbriet®
(pirfenidone)
tablets

801 mg

Keep out of reach of children.

Rx only
90 tablets

Genentech

10190516